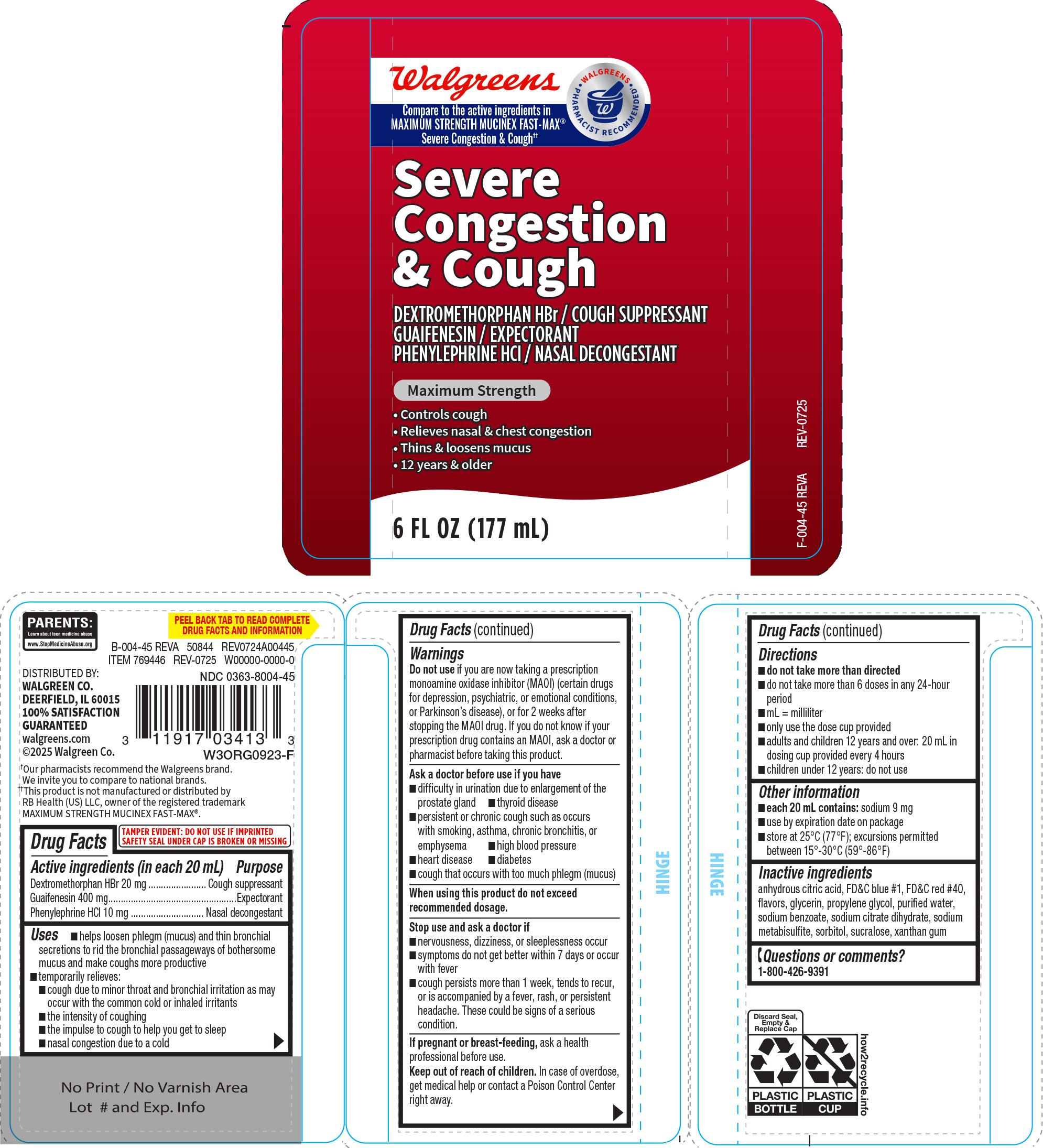 DRUG LABEL: Severe Congestion and Cough
NDC: 0363-8004 | Form: SOLUTION
Manufacturer: Walgreen Company
Category: otc | Type: HUMAN OTC DRUG LABEL
Date: 20251124

ACTIVE INGREDIENTS: DEXTROMETHORPHAN HYDROBROMIDE 20 mg/20 mL; GUAIFENESIN 400 mg/20 mL; PHENYLEPHRINE HYDROCHLORIDE 10 mg/20 mL
INACTIVE INGREDIENTS: ANHYDROUS CITRIC ACID; FD&C BLUE NO. 1; FD&C RED NO. 40; GLYCERIN; PROPYLENE GLYCOL; WATER; SODIUM BENZOATE; TRISODIUM CITRATE DIHYDRATE; SODIUM METABISULFITE; SORBITOL; SUCRALOSE; XANTHAN GUM

Walgreens 44-004

Active ingredients (in each 20 mL)

Dextromethorphan HBr 20 mg
Guaifenesin 400 mg
Phenylephrine HCl 10 mg

Purpose

Cough suppressant
Expectorant
Nasal decongestant

Uses

- helps loosen phlegm (mucus) and thin bronchial secretions to rid the bronchial passageways of bothersome mucus and make coughs more productive
- temporarily relieves:
  - cough due to minor throat and bronchial irritation as may occur with the common cold or inhaled irritants
  - the intensity of coughing
  - the impulse to cough to help you get to sleep
  - nasal congestion due to a cold

Warnings

Do not use

if you are now taking a prescription monoamine oxidase inhibitor (MAOI) (certain drugs for depression, psychiatric, or emotional conditions, or Parkinson’s disease), or for 2 weeks after stopping the MAOI drug. If you do not know if your prescription drug contains an MAOI, ask a doctor or pharmacist before taking this product.

Ask a doctor before use if you have

- high blood pressure
- thyroid disease
- difficulty in urination due to enlargement of the prostate gland
- heart disease
- diabetes
- persistent or chronic cough such as occurs with smoking, asthma, chronic bronchitis, or emphysema
- cough that occurs with too much phlegm (mucus)

When using this product

do not exceed recommended dosage.

Stop use and ask a doctor if

- nervousness, dizziness, or sleeplessness occur
- symptoms do not get better within 7 days or occur with fever
- cough persists more than 1 week, tends to recur, or is accompanied by a fever, rash, or persistent headache. These could be signs of a serious condition.

If pregnant or breast-feeding,

ask a health professional before use.

Keep out of reach of children.

In case of overdose, get medical help or contact a Poison Control Center right away.

Directions

- do not take more than directed
- do not take more than 6 doses in any 24-hour period
- mL = milliliter
- only use the dose cup provided
- adults and children 12 years and over: 20 mL in dosing cup provided every 4 hours
- children under 12 years: do not use

Other information

- each 20 mL contains: sodium 9 mg
- store at 25°C (77°F); excursions permitted between 15°-30°C (59°-86°F)
- use by expiration date on package

Inactive ingredients

anhydrous citric acid, FD&C blue #1, FD&C red #40, flavors, glycerin, propylene glycol, purified water, sodium benzoate, sodium citrate dihydrate, sodium metabisulfite, sorbitol, sucralose, xanthan gum

Questions or comments?

1-800-426-9391

Principal Display Panel

NDC 0363-8004-45

Walgreens

• WALGREENS •
PHARMACIST RECOMMENDED†

Compare to the active ingredients in
MAXIMUM STRENGTH MUCINEX FAST-MAX®
Severe Congestion & Cough††

Severe
Congestion
& Cough
DEXTROMETHORPHAN HBr / COUGH SUPPRESSANT
GUAIFENESIN / EXPECTORANT
PHENYLEPHRINE HCl / NASAL DECONGESTANT

Maximum Strength

• Controls cough
• Relieves nasal & chest congestion
• Thins & loosens mucus
• 12 years & older

6 FL OZ (177 mL)

TAMPER EVIDENT: DO NOT USE IF IMPRINTED
SAFETY SEAL UNDER CAP IS BROKEN OR MISSING

PARENTS:
Learn about teen medicine abuse
www.StopMedicineAbuse.org

B-004-45 REVA 50844 REV0724A00445

DISTRIBUTED BY:
WALGREEN CO.
DEERFIELD, IL 60015
100% SATISFACTION
GUARANTEED
walgreens.com
©2025 Walgreen Co.

†Our pharmacists recommend the Walgreens brand.
We invite you to compare to national brands.

††This product is not manufactured or distributed by
RB Health (US) LLC, owner of the registered trademark
MAXIMUM STRENGTH MUCINEX FAST-MAX®.

Walgreens 44-004